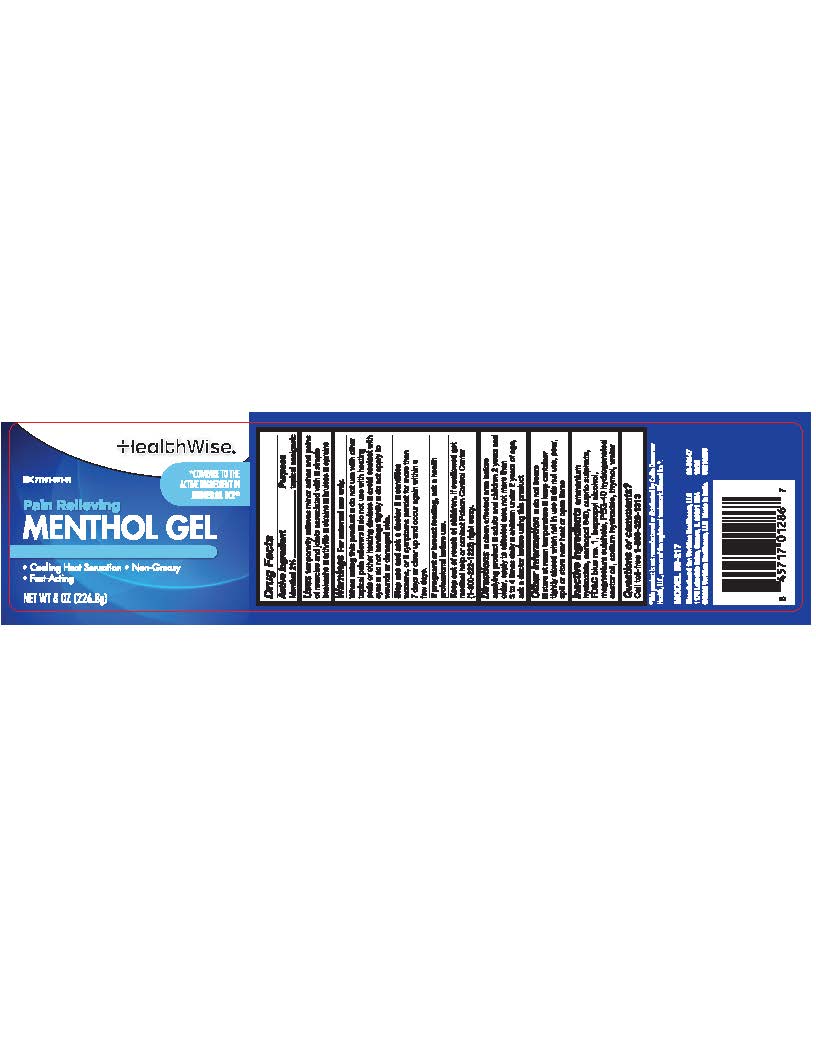 DRUG LABEL: HealthWise Pain Relieving Menthol Gel
NDC: 71101-091 | Form: GEL
Manufacturer: Veridian Healthcare
Category: otc | Type: HUMAN OTC DRUG LABEL
Date: 20251222

ACTIVE INGREDIENTS: MENTHOL 2 g/1 mL
INACTIVE INGREDIENTS: AMMONIA; CARBOMER HOMOPOLYMER TYPE C (ALLYL PENTAERYTHRITOL CROSSLINKED); CUPRIC SULFATE; FD&C BLUE NO. 1; ISOPROPYL ALCOHOL; MAGNESIUM SULFATE ANHYDROUS; THYMOL; WATER; SODIUM HYDROXIDE; PEG-40 HYDROGENATED CASTOR OIL

HealthWise Pain Relieving Menthol Gel

Drug Facts

Active Ingredient

Menthol 2%

Purpose

- Topical Analgesic

Uses

Uses Temporary relief from minor aches and pains of sore muscles and joints associated with:

■arthritis ■backache ■strains■sprains

Warnings

For external use only

When using this product, do not

When using this product:

■ do not use with other topical pain relievers

■do not use with a heating pads or other heating devices

■ avoid contact with eyes

■do not bandage tightly

■ do not apply to wounds or damaged skin

Stop use and ask a doctor if: the condition worsens, or if symptoms persist for more than 7 days or clear up and occur again withing a few days.

PREGNANCY OR BREAST FEEDING

If pregnant or breast-feeding,ask a health professional before use.

Keep out of reach of children. In case of accidental ingestion, get medical help orcontact a Poison Control Center (800-222-1222) right away.

Directions

- clean affected area before applying product
- Adults and children 2 years of age and older apply to the affected area not more than 3 to 4 times daily
- Children under 2 years of age, ask a doctor before using this product

Other information

- do not freeze
- store at room temperature
- keep container tightly closed when not in use
- do not use, pour, spill or store near heat or open flame

Inactive ingredients

ammonium hydroxide, carbopol 940, cupric sulfate, FD&C blue No. 1, Isopropyl alcohol, magnesium sulphate, PEG-40 hydrogenated castor oil sodium hydroxide, thymol, water